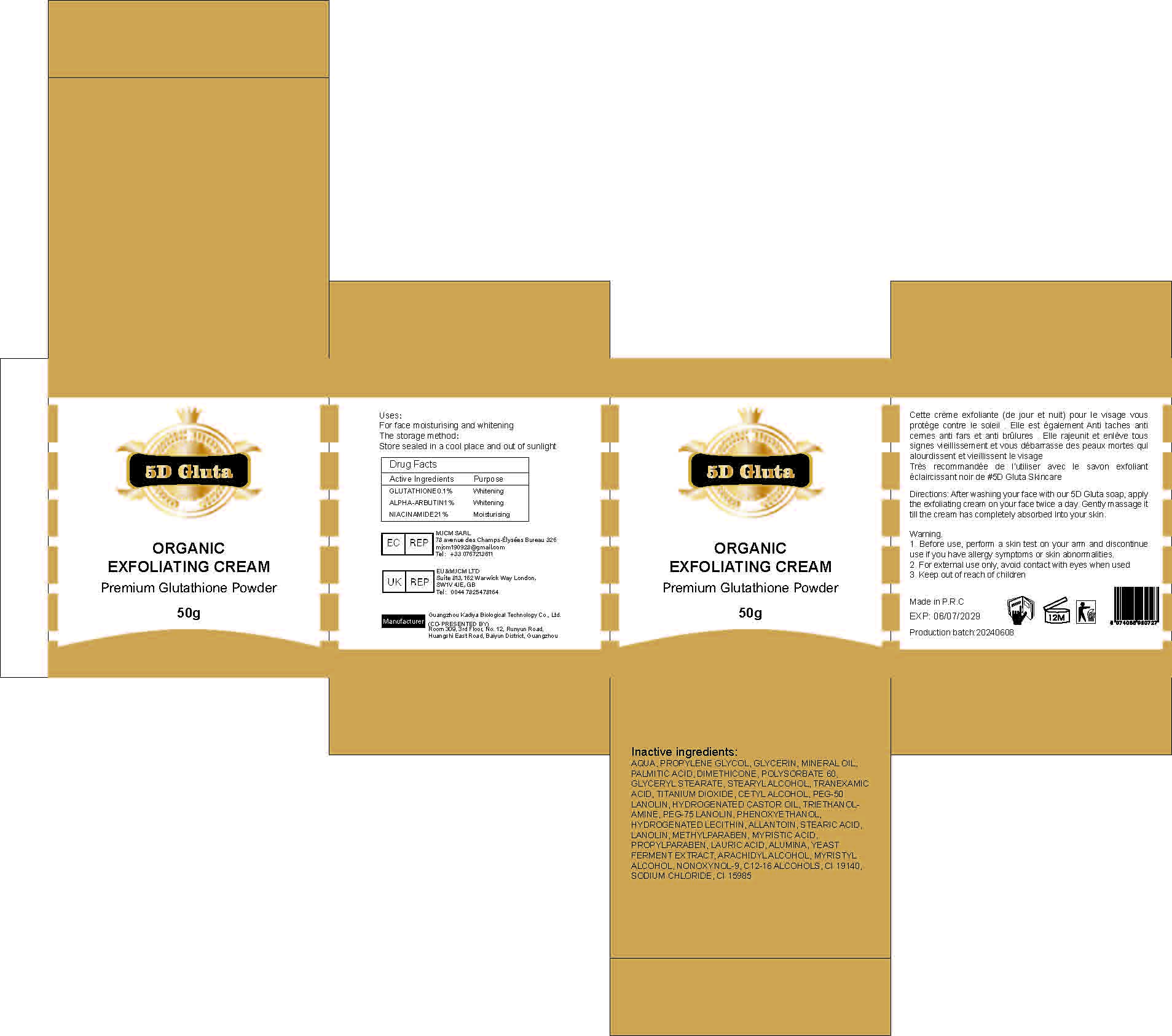 DRUG LABEL: 5D Gluta Organic Exfoliating Cream Premium Glutathione Powder
NDC: 84423-005 | Form: EMULSION
Manufacturer: Guangzhou Kadiya Biotechnology Co. Ltd.
Category: otc | Type: HUMAN OTC DRUG LABEL
Date: 20240628

ACTIVE INGREDIENTS: ALPHA-ARBUTIN 0.01 g/50 g; GLUTATHIONE 0.001 g/50 g; NIACINAMIDE 0.2 g/50 g
INACTIVE INGREDIENTS: DIMETHICONE; FD&C YELLOW NO. 5; MYRISTYL ALCOHOL; STEARYL ALCOHOL; ARACHIDYL ALCOHOL; C12-16 ALCOHOLS; WATER; GLYCERIN; TITANIUM DIOXIDE; TROLAMINE; ALUMINUM OXIDE; SODIUM CHLORIDE; FD&C YELLOW NO. 6; NONOXYNOL-9; PROPYLENE GLYCOL; MINERAL OIL; PALMITIC ACID; STEARIC ACID; POLYSORBATE 60; MYRISTIC ACID; PEG-50 LANOLIN; ALLANTOIN; LANOLIN; GLYCERYL MONOSTEARATE; LAURIC ACID; TRANEXAMIC ACID; HYDROGENATED CASTOR OIL; PROPYLPARABEN; CETYL ALCOHOL

Active Ingredients

GLUTATHIONE0.1%
ALPHA-ARBUTIN1%
NIACINAMIDE 21%

Purpose

For face moisturising and whitening

INACTIVE INGEDIENT

AQUA, PROPYLENE GLYCOL, GLYCERIN, MINERAL OIL, PALMITIC ACID, DIMETHICONE, POLYSORBATE 60, GLYCERYL STEARATE, STEARYL ALCOHOL, TRANEXAMIC ACID, TITANIUM DIOXIDE, CETYL ALCOHOL, PEG-50 LANOLIN, HYDROGENATED CASTOR OIL, TRIETHANOLAMINE, PEG-75 LANOLIN, PHENOXYETHANOL, HYDROGENATED LECITHIN, ALLANTOIN, STEARIC ACID, LANOLIN, MYRISTIC ACID, PROPYLPARABEN, ALUMINA, YEAST FERMENT EXTRACT, ARACHIDYL ALCOHOL, MYRISTYL ALCOHOL, NONOXYNOL-9, C12-16 ALCOHOLS, CI 19140,
SODIUM CHLORIDE, CI 15985

WARNING

1. Before use, perform a skin test on your arm and discontinue
use if you have allergy symptoms or skin abnormalities.
2. For external use only, avoid contact with eyes when used
3. Keep out of reach of children

INSTRUCTIONS FOR USE

After washing your face with our 5D Gluta soap, apply
the exfoliating cream on your face twice a day. Gently massage it
till the cream has completely absorbed into your skin.

Dosage

After washing your face with our 5D Gluta soap, apply the exfoliating cream on your face twice a day. Gently massage it till the cream has completely absorbed into your skin.

USAGE

For external use only, avoid contact with eyes when used

Warning

out of reach of children

PACKAGE LABEL

5D Gluta Organic Exfoliating Cream Premium Glutathione Powder

1. Active Ingredients
GLUTATHIONE0.1%
ALPHA-ARBUTIN1%
NIACINAMIDE 21%

2.Purpose
For face moisturising and whitening

3.Inactive ingredients:
AQUA, PROPYLENE GLYCOL, GLYCERIN, MINERAL OIL, PALMITIC ACID, DIMETHICONE, POLYSORBATE 60, GLYCERYL STEARATE, STEARYL ALCOHOL, TRANEXAMIC ACID, TITANIUM DIOXIDE, CETYL ALCOHOL, PEG-50 LANOLIN, HYDROGENATED CASTOR OIL, TRIETHANOLAMINE, PEG-75 LANOLIN, PHENOXYETHANOL, HYDROGENATED LECITHIN, ALLANTOIN, STEARIC ACID, LANOLIN, MYRISTIC ACID, PROPYLPARABEN, ALUMINA, YEAST FERMENT EXTRACT, ARACHIDYL ALCOHOL, MYRISTYL ALCOHOL, NONOXYNOL-9, C12-16 ALCOHOLS, CI 19140,
SODIUM CHLORIDE, CI 15985

4.Warning
1. Before use, perform a skin test on your arm and discontinue
use if you have allergy symptoms or skin abnormalities.
2. For external use only, avoid contact with eyes when used
3. Keep out of reach of children

5.Instructions for use
After washing your face with our 5D Gluta soap, apply
the exfoliating cream on your face twice a day. Gently massage it
till the cream has completely absorbed into your skin.